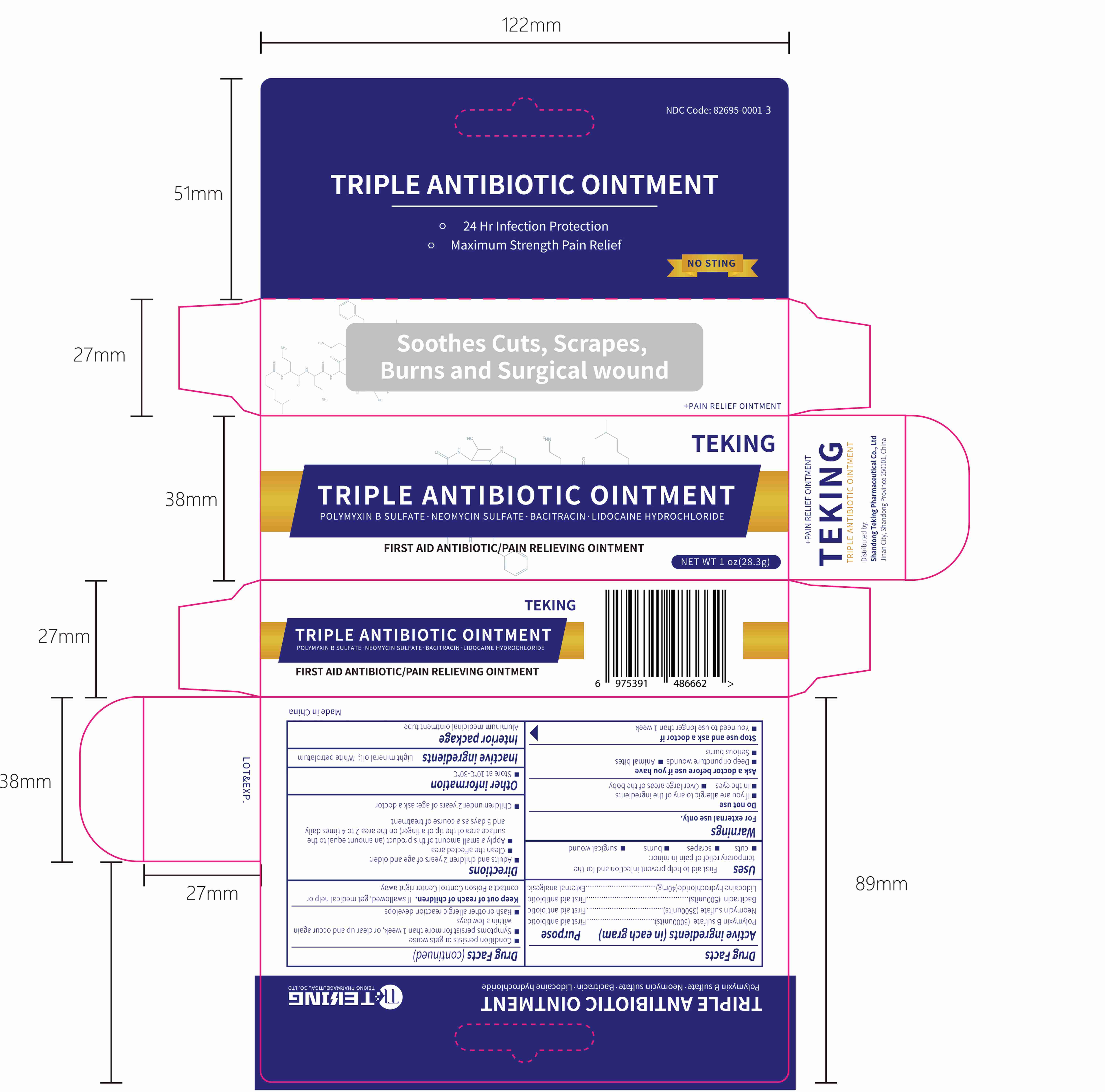 DRUG LABEL: TRIPLE ANTIBIOTIC
NDC: 82695-0001 | Form: OINTMENT
Manufacturer: Shandong Teking Pharmaceutical Co., Ltd
Category: otc | Type: HUMAN OTC DRUG LABEL
Date: 20221025

ACTIVE INGREDIENTS: POLYMYXIN B SULFATE 5000 [USP'U]/1 g; NEOMYCIN SULFATE 3500 [USP'U]/1 g; BACITRACIN 500 [USP'U]/1 g; LIDOCAINE 40 mg/1 g
INACTIVE INGREDIENTS: LIGHT MINERAL OIL; WHITE PETROLATUM

ACTIVE INGREDIENT

Polymyxin B sulfate 5000units

Neomycin sulfate 3500units

Bacitracin 500units

Lidocaine hydrochloride 40mg

PURPOSE

First aid antibiotic

First aid antibiotic

First aid antibiotic

External analgesic

INDICATIONS AND USAGE

First aid to help prevent infection and for the temporary relief of pain in minor:

- cuts
- scrapes
- burns
- surgical wound

WARNINGS

For external use only

DO NOT USE

- If you are allergic to any of the ingredients
- In the eyes
- Over large areas of the body

ASK DOCTOR

- Deep or puncture wounds
- Animal bites
- Serious burns

- You need to use longer than 1 week
- Condition persists or gets worse
- Symptoms persist for more than 1 week, or clear up and occur again within a few days
- Rash or other allergic reaction develops

KEEP OUT OF REACH OF CHILDREN

If swallowed, get medical help or contact a Poison Control Center right away.

DOSAGE AND ADMINISTRATION

- Adults and children 2 years of age and older:

- Clean the affected area;

- Apply a small amount of this product (an amount equal to the surface area of the tip of a finger) on the area 2 to 4 times daily and 5 days as a course of treatment.

- Children under 2 years of age: ask a doctor

OTHER SAFETY INFORMATION

- Store at 10℃-30℃

INACTIVE INGREDIENT

Light mineral oil

White petrolatum

PACKAGE LABEL

TRIPLE ANTIBIOTIC OINTMENT